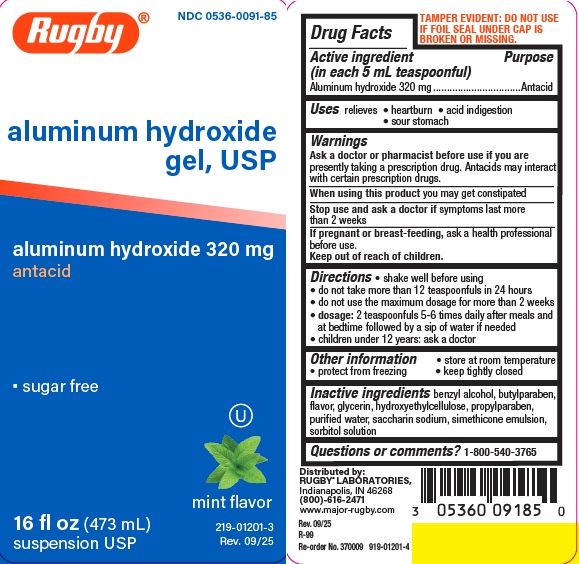 DRUG LABEL: Aluminum Hydroxide
NDC: 0536-0091 | Form: LIQUID
Manufacturer: Rugby Laboratories
Category: otc | Type: HUMAN OTC DRUG LABEL
Date: 20251211

ACTIVE INGREDIENTS: ALUMINUM HYDROXIDE 320 mg/5 mL
INACTIVE INGREDIENTS: BENZYL ALCOHOL; BUTYLPARABEN; GLYCERIN; HYDROXYETHYLCELLULOSE; DIMETHICONE; PROPYLPARABEN; WATER; SACCHARIN SODIUM; SORBITOL SOLUTION

Rugby aluminum hydroxide

Active ingredient (in each 5 mL teaspoonful)

Aluminum hydroxide 320 mg

Purpose

Antacid

Uses

relieves

- heartburn
- acid indigestion
- sour stomach

Warnings

Ask a doctor or pharmacist before use if you are taking a prescription drug.

Antacids may interact with certain prescription drugs.
When using this product you may get constipated

Stop use and ask a doctor if symptoms last more than 2 weeks

If pregnant or breast-feeding, ask a health professional
before use.

Keep out of reach of children.

Directions

- shake well before using
- do not take more than 12 teaspoonfuls in 24 hours
- do not use the maximum dosage for more than 2 weeks
- dosage: 2 teaspoonfuls 5-6 times daily after meals and at bedtime followed by a sip of water if needed
- children under 12 years: ask a doctor

Other information

- store at room temperature
- protect from freezing
- keep tightly closed

Inactive ingredients

benzyl alcohol, butylparaben, flavor, glycerin, hydroxyethylcellulose, propylparaben, purified water, saccharin sodium, simethicone emulsion, sorbitol solution

Questions or comments?

1-800-540-3765